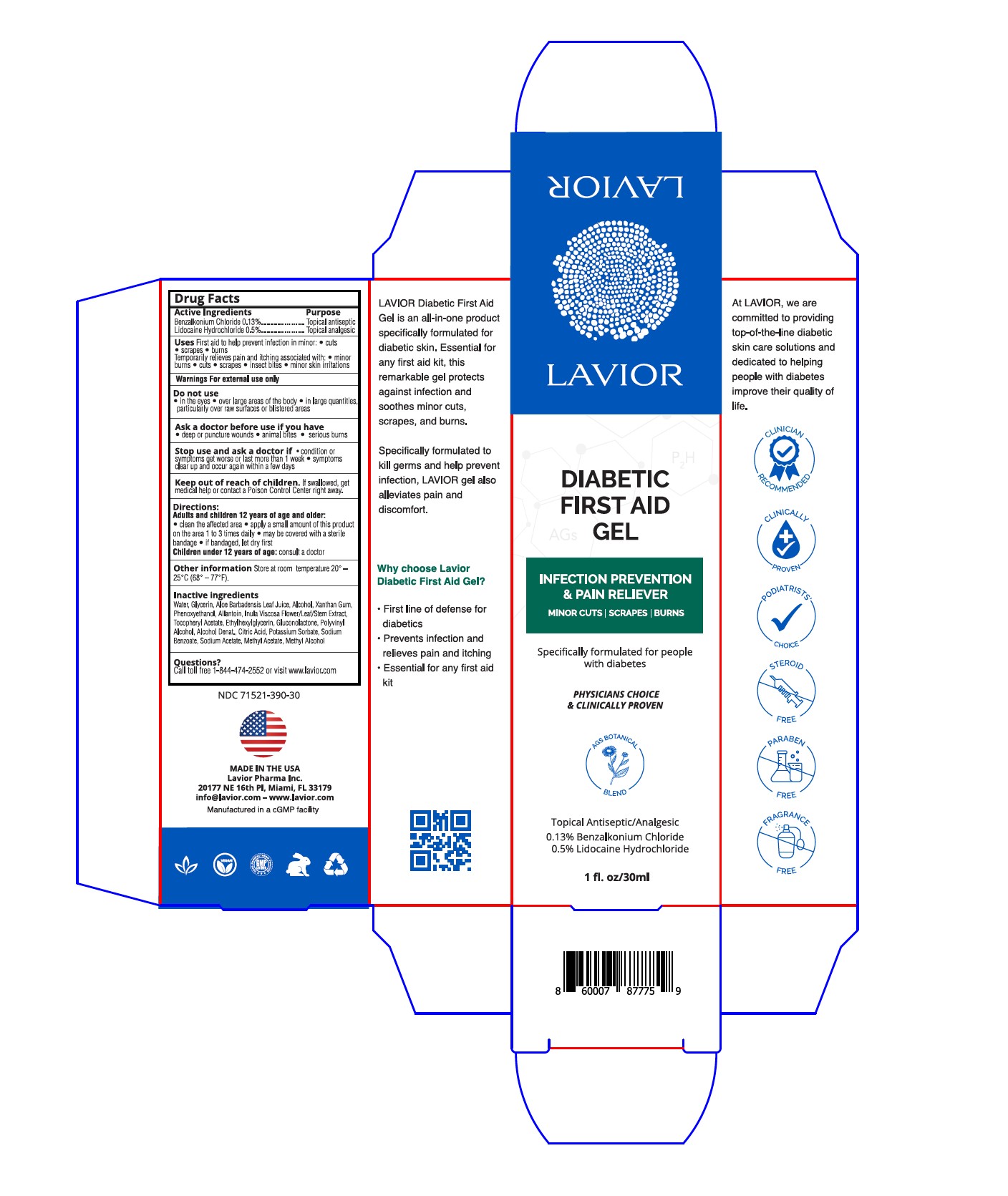 DRUG LABEL: Diabetic First Aid Gel
NDC: 71521-390 | Form: GEL
Manufacturer: Lavior Pharma Inc.
Category: otc | Type: HUMAN OTC DRUG LABEL
Date: 20241022

ACTIVE INGREDIENTS: LIDOCAINE HYDROCHLORIDE 0.5 g/100 g; BENZALKONIUM CHLORIDE 0.13 g/100 g
INACTIVE INGREDIENTS: .ALPHA.-TOCOPHEROL ACETATE; ETHYLHEXYLGLYCERIN; ALCOHOL; GLUCONOLACTONE; GLYCERIN; XANTHAN GUM; POLYVINYL ALCOHOL, UNSPECIFIED; CITRIC ACID MONOHYDRATE; SODIUM BENZOATE; ALLANTOIN; ALOE VERA LEAF; PHENOXYETHANOL; POTASSIUM SORBATE; DITTRICHIA VISCOSA WHOLE

Active Ingredients

Benzalkonium Chloride 0.13% .................Topical Antiseptic
Lidocaine Hydrochloride 0.5% .................Topical Analgesic

Purpose

Topical Antiseptic
Topical Analgesic

Uses

First aid to help prevent infection in minor:

■cuts ■scrapes ■burns

Temporarily relieves pain and itching associated with:

■minor burns ■cuts ■scrapes ■insect bites ■minor skin irritations

Warnings

For external use only

Do not use

- in the eyes
- over large areas of the body
- in large quantities, particularly over raw surfaces or blistered areas

Ask a doctor before use if you have

- deep or puncture wounds
- animal bites
- serious burns

Stop use and ask a doctor if

- condition or symptoms get worse or last more than 1 week
- symptoms clear up and occur again within a few days

Keep out of reach of children

If swallowed, get medical help or contact a Poison Control Center right away.

Directions

Adults and children 12 years of age and older:

- clean the affected area
- apply a small amount of this product on the area 1 to 3 times daily
- may be covered with a sterile bandage
- if bandaged, let dry first

Children under 12 years of age: consult a doctor

Other information

Store at room temperature

Inactive Ingredients

Water, Glycerin, Inula Viscosa Flower/Leaf/Stem Extract, Aloe Barbadensis Leaf Juice, Xanthan Gum, Phenoxyethanol, Allantoin, Tocopheryl Acetate, Ethylhexylglycerin, Gluconolactone, Polyvinyl Alcohol, Alcohol, Citric Acid, Sodium Benzoate, Potassium Sorbate

Questions?

Call (305) 627-3680 or visit www.lavior.com